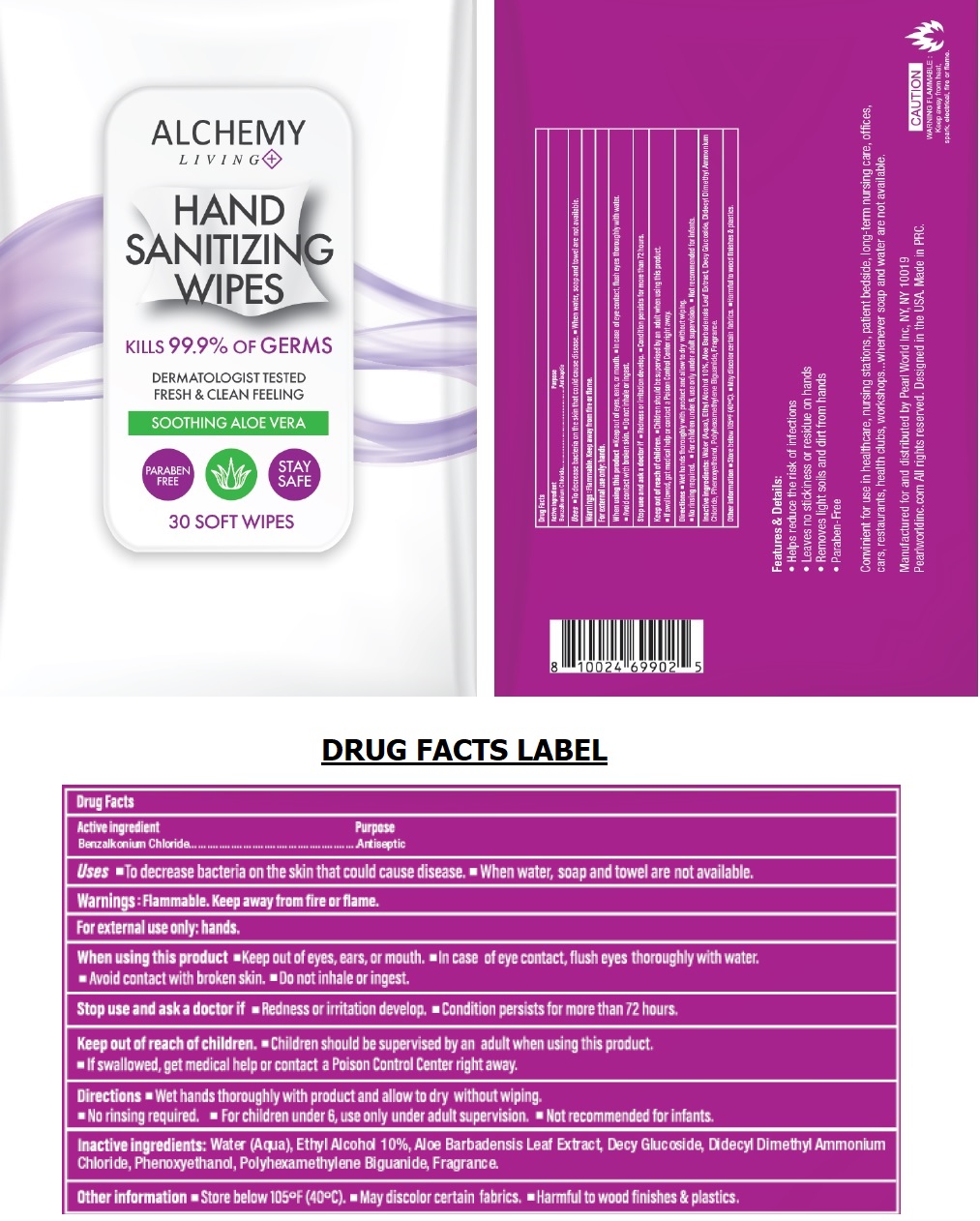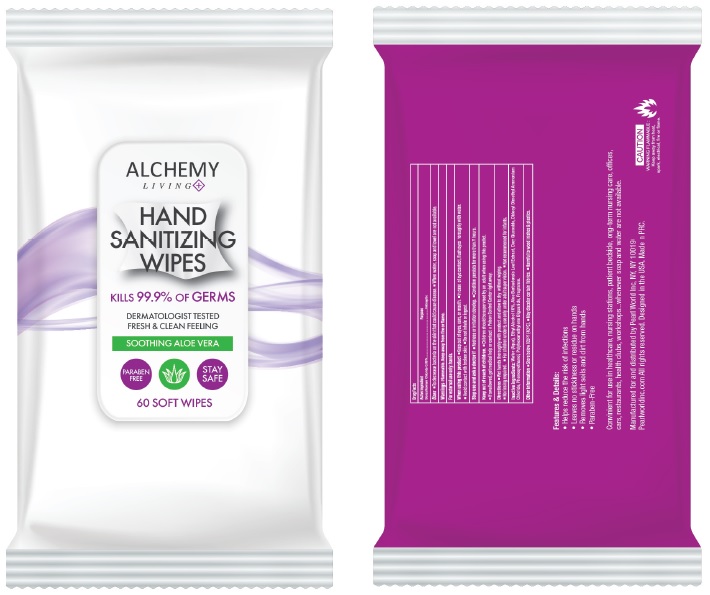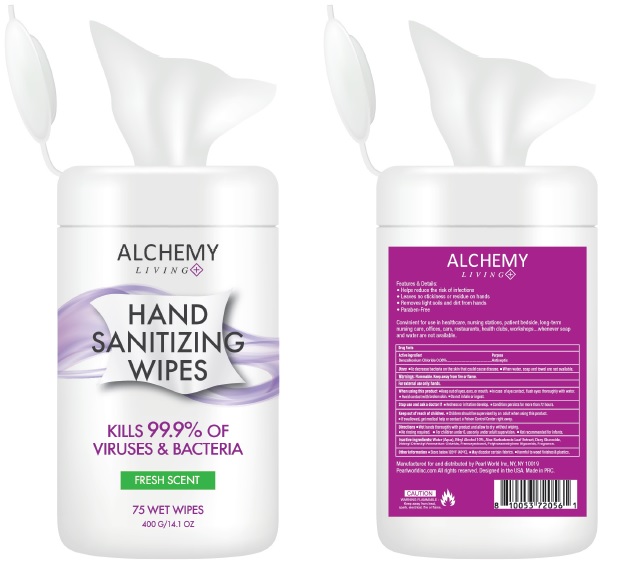 DRUG LABEL: Alchemy Living Hand Sanitizing Wipes
NDC: 69933-302 | Form: CLOTH
Manufacturer: Pearl World Inc.
Category: otc | Type: HUMAN OTC DRUG LABEL
Date: 20200720

ACTIVE INGREDIENTS: BENZALKONIUM CHLORIDE 0.08 g/100 g
INACTIVE INGREDIENTS: WATER; ALCOHOL; ALOE VERA LEAF; DECYL GLUCOSIDE; DIDECYLDIMONIUM CHLORIDE; PHENOXYETHANOL; POLIHEXANIDE

ALCHEMY LIVING HAND SANITIZING WIPES

Active ingredient

Benzalkonium Chloride

Purpose

Antiseptic

INDICATIONS AND USAGE

Uses ■To decrease bacteria on the skin that could cause disease. ■ When water, soap and towel are not available.

Warnings : Flammable. Keep away from fire or flame.

For external use only: hands

When using this product ■Keep out of eyes, ears, or mouth. ■In case of eye contact, flush eyes

thoroughly with water. ■Avoid contact with broken skin. ■Do not inhale or ingest.

Stop use and ask a doctor if ■Redness or irritation develop. ■Condition persists for more than 72 hours.

Keep out of reach of children. ■Children should be supervised by an adult when using this product.

■If swallowed, get medical help or contact a Poison Control Center right away.

DOSAGE AND ADMINISTRATION

Directions ■Wet hands thoroughly with product and allow to dry without wiping. ■No rinsing required.

■For children under 6, use only under adult supervision ■Not recommended for infants.

Other information ■ Store below 105°F (40°C). ■ May discolor certain fabrics. ■ Harmful to wood finishes & plastics.

INACTIVE INGREDIENT

Inactive ingredients: Water (Aqua), Ethyl Alcohol 10%, Aloe Barbadensis Leaf Extract, Decyl Glucoside, Didecyl Dimethyl Ammonium Chloride, Phenoxyethanol, Polyhexamethylene Biguanide, Fragrance.

KILLS 99.9% OF GERMS

DERMATOLOGIST TESTED

FRESH & CLEAN FEELING

SOOTHING ALOE VERA

PARABEN FREE

STAY SAFE

Features & Details:

• Helps reduce the risk of infections

• Leaves no stickiness or residue on hands

• Removes light soils and dirt from hands

• Paraben-Free

Convenient for use in healthcare, nursing stations, patient bedside, long-term nursing care, offices, cars, restaurants, health clubs, workshops....whenever soap and water are not available.

Manufactured for and distributed by Pearl world Inc, NY, NY 10019

Pearlworldinc.com All rights reserved. Designed in the USA. Made in PRC.

CAUTION

WARNING FLAMMABLE:

Keep away from heat, spark, electrical, fire or flame.